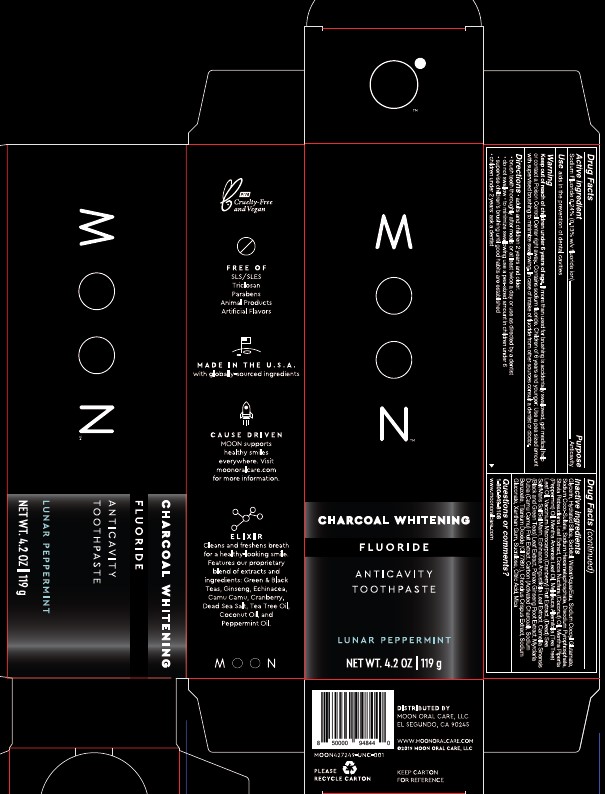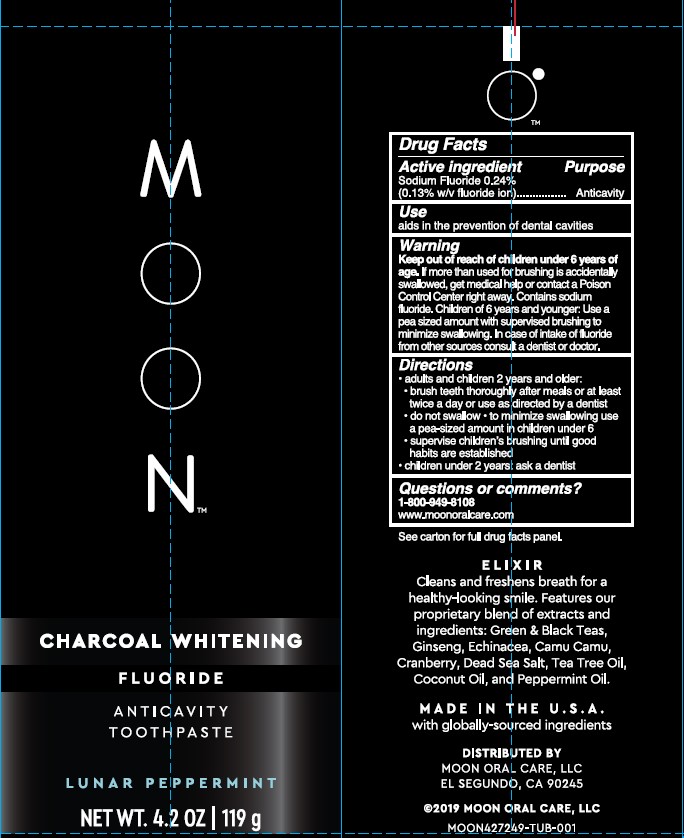 DRUG LABEL: Moon Charcoal Whitening Anticavity
NDC: 82214-003 | Form: PASTE
Manufacturer: Moon Oral Care, LLC
Category: otc | Type: HUMAN OTC DRUG LABEL
Date: 20231212

ACTIVE INGREDIENTS: SODIUM FLUORIDE 0.24 g/100 g
INACTIVE INGREDIENTS: SODIUM BENZOATE; CARBOXYMETHYLCELLULOSE SODIUM, UNSPECIFIED; CITRIC ACID MONOHYDRATE; MICA; SODIUM ACID PYROPHOSPHATE; COCONUT OIL; TEA TREE OIL; CRANBERRY SEED OIL; GREEN TEA LEAF; ASIAN GINSENG; STEVIA REBAUDIUNA LEAF; SEA SALT; SUCRALOSE; SODIUM COCO-SULFATE; SORBITOL; SODIUM COCOYL GLUTAMATE; SODIUM POLYMETAPHOSPHATE; ECHINACEA ANGUSTIFOLIA LEAF; ACTIVATED CHARCOAL; CHONDRUS CRISPUS CARRAGEENAN; PEPPERMINT OIL; MENTHA ARVENSIS LEAF OIL; MYRCIARIA DUBIA FRUIT; TITANIUM DIOXIDE; GLYCERIN; SODIUM GLUCONATE; HYDRATED SILICA; WATER

Active Ingredient: Sodium Fluoride 0.24% (0.13% w/v fluoride ion) Anticavity

PURPOSE

Use aids in the prevention of dental cavities

Keep out of reach of children under 6 years of age. If more than used for brushing is accidentally swallowed, get medical help or contact a Poison Control Center right away.

INDICATIONS AND USAGE

Children of 6 years and younger: Use a pea sized amount with supervised brushing to minimize swallowing.

Warning

Contains Sodium Fluoride. In case of intake of fluoride from other sources consult a dentist or doctor.

Directions:

Adults and children 2 years and older:

brush teeth thoroughly after meals or at least twice a day or use as directed by a dentist

do not swallow

to minimize swallowing use a pea-sized amount in children under 6

supervise children's brushing until good habits are established

children under 2 years: ask a dentist

Inactive ingredients:

Glycerin, Hydrated Silica, Sorbitol, Water/Aqua/Eau, Sodium Cocoyl Glutamate, Sodium Coco-Sulfate, Sodium Hexametaphosphate, Disodium Pyrophosphate, Stevia Rebaudiana Leaf Extract, Cocos Nucifera (Coconut) Oil, Mentha Piperita (Peppermint) Oil, Mentha Arvensis Leaf Oil, Melaleuca Alternifolia (Tea Tree) Leaf Oil, Vaccinium Macrocarpon (Cranberry) Fruit Extract, Sea Salt, Echinacea Angustifolia Leaf Extract, Camellia Sinensis (Black and Green Teas) Leaf Extract, Panax Ginseng Root Extract, Mrciaria Dubia (Camu Camu) Fruit Extract, Carbon (Activated Charcoal), Sodium Benzoate, Titanium Dioxide, Chondrus Crispus Extract, Sodium Gluconate, Xanthan Gum, Sucralose, Citric Acid, Mica